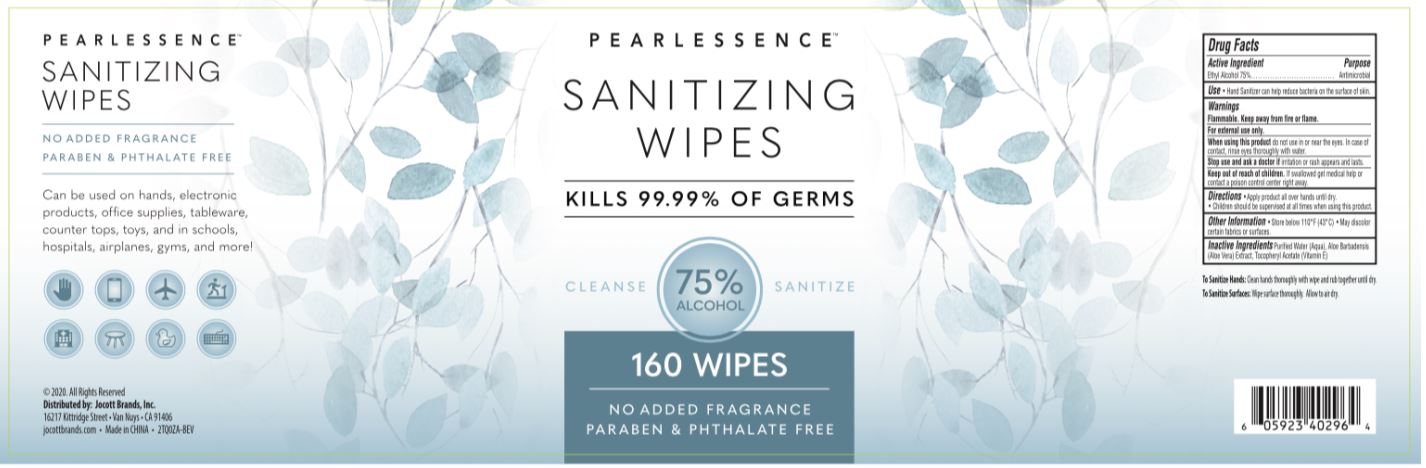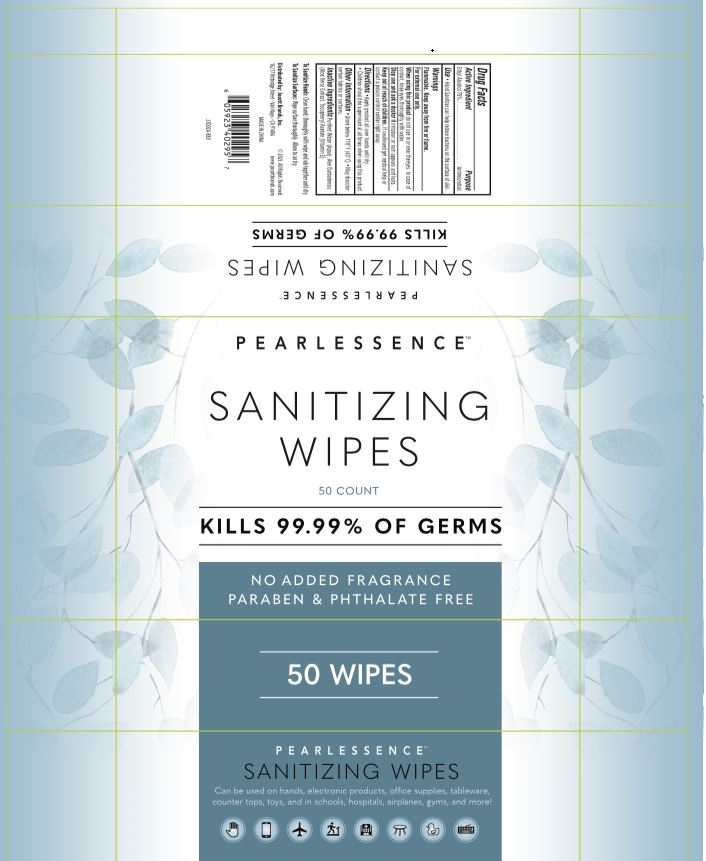 DRUG LABEL: PEARLESSENCE SANITIZING WIPES
NDC: 78902-302 | Form: SOLUTION
Manufacturer: Jocott Brands, Inc.
Category: otc | Type: HUMAN OTC DRUG LABEL
Date: 20201109

ACTIVE INGREDIENTS: ALCOHOL 7.5 mL/1 1
INACTIVE INGREDIENTS: WATER; ALOE VERA LEAF; .ALPHA.-TOCOPHEROL ACETATE

PEARLESSENCE - SANITIZING WIPES - 75% Ethyl Alcohol

ACTIVE INGREDIENT

ETHYL ALCOHOL 75%

PURPOSE

ANTIMICROBIAL

USE

- HAND SANITIZER CAN HELP REDUCE BACTERIA ON THE SURFACE OF SKIN.

WARNINGS

FLAMMABLE. KEEP AWAY FROM FIRE OR FLAME.

FOR EXTERNAL USE ONLY.

WHEN USING THIS PRODUCT DO NOT USE IN OR NEAR THE EYES. IN CASE OF CONTACT, RINSE EYES THOROUGHLY WITH WATER.

STOP USE AND ASK A DOCTOR IF IRRITATION OR RASH APPEARS AND LASTS.

KEEP OUT OF REACH OF CHILDREN. IF SWALLOWED GET MEDICAL HELP OR CONTACT A POISON CONTROL CENTER RIGHT AWAY.

DIRECTIONS

- APPLY PRODUCT ALL OVER HANDS UNTIL DRY.
- CHILDREN SHOULD BE SUPERVISED AT ALL TIMES WHEN USING THIS PRODUCT.

OTHER INFORMATION

- STORE BELOW 110°F (43°C)
- MAY DISCOLOR CERTAIN FABRICS OR SURFACES

INACTIVE INGREDIENTS

Purified Water (Aqua), Aloe Barbadensis (Aloe Vera) Leaf Juice, Tocopheryl Acetate (Vitamin E)